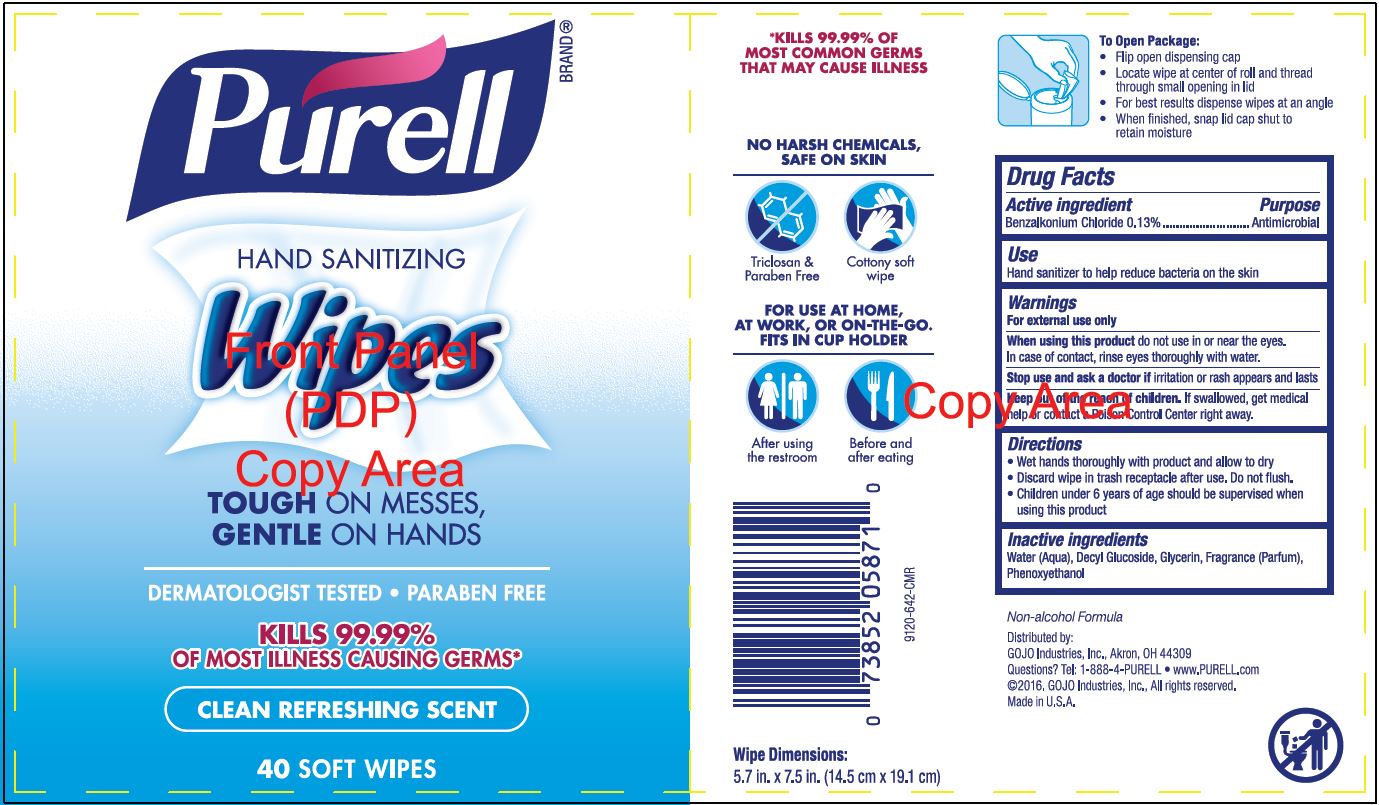 DRUG LABEL: PURELL Hand Sanitizing Wipes Clean Refreshing Scent
NDC: 21749-359 | Form: CLOTH
Manufacturer: GOJO Industries, Inc.
Category: otc | Type: HUMAN OTC DRUG LABEL
Date: 20241212

ACTIVE INGREDIENTS: BENZALKONIUM CHLORIDE 0.13 mg/100 mL
INACTIVE INGREDIENTS: WATER; DECYL GLUCOSIDE; GLYCERIN; PHENOXYETHANOL

PURELL Hand Sanitizing Wipes Clean Refreshing Scent

Active ingredient

Benzalkonium Chloride 0.13%

Active ingredient

Benzalkonium Chloride 0.13%

Purpose

Antimicrobial

Use

Hand sanitizer to help reduce bacteria on the skin

Warnings

For external use only

WHEN USING

When using this productdo not use in or near the eyes. In case of contact, rinse eyes thoroughly with water.

Stop use and ask a doctor ifirritation or rash appears and lasts

Keep out of reach of children.If swallowed, get medical help or contact a Poison Control Center right away.

Directions

• Wet hands thoroughly with product and allow to dry

• Children under 6 years of age should be supervised when using PURELL

Inactive ingredients

Water (Aqua), Decyl Glucoside, Glycerin, Fragrance(Parfum), Phenoxyethanol